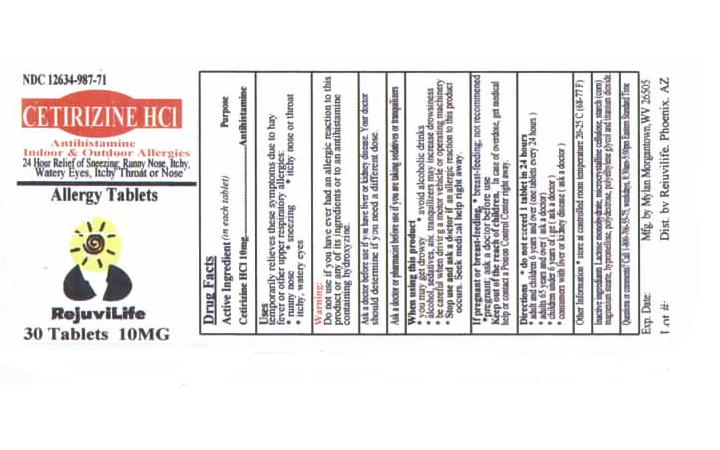 DRUG LABEL: CETIRIZINE HYDROCHLORIDE
NDC: 12634-987 | Form: TABLET
Manufacturer: Apotheca Inc.
Category: otc | Type: HUMAN OTC DRUG LABEL
Date: 20100407

ACTIVE INGREDIENTS: CETIRIZINE HYDROCHLORIDE 10 mg/1 1
INACTIVE INGREDIENTS: CELLULOSE, MICROCRYSTALLINE; MAGNESIUM STEARATE; HYPROMELLOSE; TITANIUM DIOXIDE

Cetirizine 10mg Tablets, Allergy Tablets DRUG FACTS

ACTIVE INGREDIENT

(in each Tablet)
Cetirizine HCI 10mg

PURPOSE

ANTIHISTAMINE
24 Hour Relief of Indoor and Outdoor Allergies

USES

Temporarily relieves these symptoms due to hay fever or other upper respiratory allergies

- runny nose
- sneezing
- itchy, watery eyes
- itching of the nose or throat

WARNINGS

Do Not Use if you have ever had an allergic reaction to this product or any of its ingredients or to an antihistamine containing hydroxyzine.

Ask a Doctor before use

if you have liver or kidney disease. Your doctor should determine if you need a different dose.

Ask a Doctor or Pharmacist before use

if you are taking tranquilizers or sedatives.

When using this product

- drowsines may occur
- avoid alcoholic drinks
- alcohol, sedatives, and tranquilizers may increase drowsiness
- be careful when driving a motor vehicle or operating machinary.

Stop use and ask a doctor

if an allergic reaction to this product occurs. Seek medical help right away.

If pregnant or breast-feeding:

- if breast-feeding: not recommended
- if pregnant: ask a health professional before use.

Keep out of reach of children.

In case of overdose, get medical help or contact Poison Control Center right away.

Directions

Adults and children 6 years and over | one 10 mg tablet once daily, do not take more than one 10 mg tablet in 24 hours.
Adults 65 years and over | Ask a doctor
Children under 6 years of age | Ask a doctor
Consumers with liver or kidney disease | Ask a doctor

Other information and inactive ingredients

Other information

- store between 20° to 25°C (68° to 77°F)

Inactive ingredients

anhydrous lactose, colloidal silicon dioxide, hypromellose, magnesium stearate, microcrystalline cellulose, polydextrose, polyethylene glycol, sodium lauryl sulfate, titanium dioxide, and triacetin

Questions

Call 1-800-262-5244

Monday though Friday 9AM – 2PM MST

Distributed by:

RejuviLife, Phoenix, AZ

RejuviLife is a trademark of Apotheca Inc.

PACKAGE LABEL AND PRINCIPAL DISPLAY PANEL

NDC 12634-987-71
CETIRIZINE HCI
Antihistamine
Indoor and Outdoor Allergies
24 Hour Relief of Sneezing, Runny Nose, Itchy,
Watery Eyes, Itchy Throat or Nose.
Allergy Tablets
RejuviLife
30 Tablets
10 MG